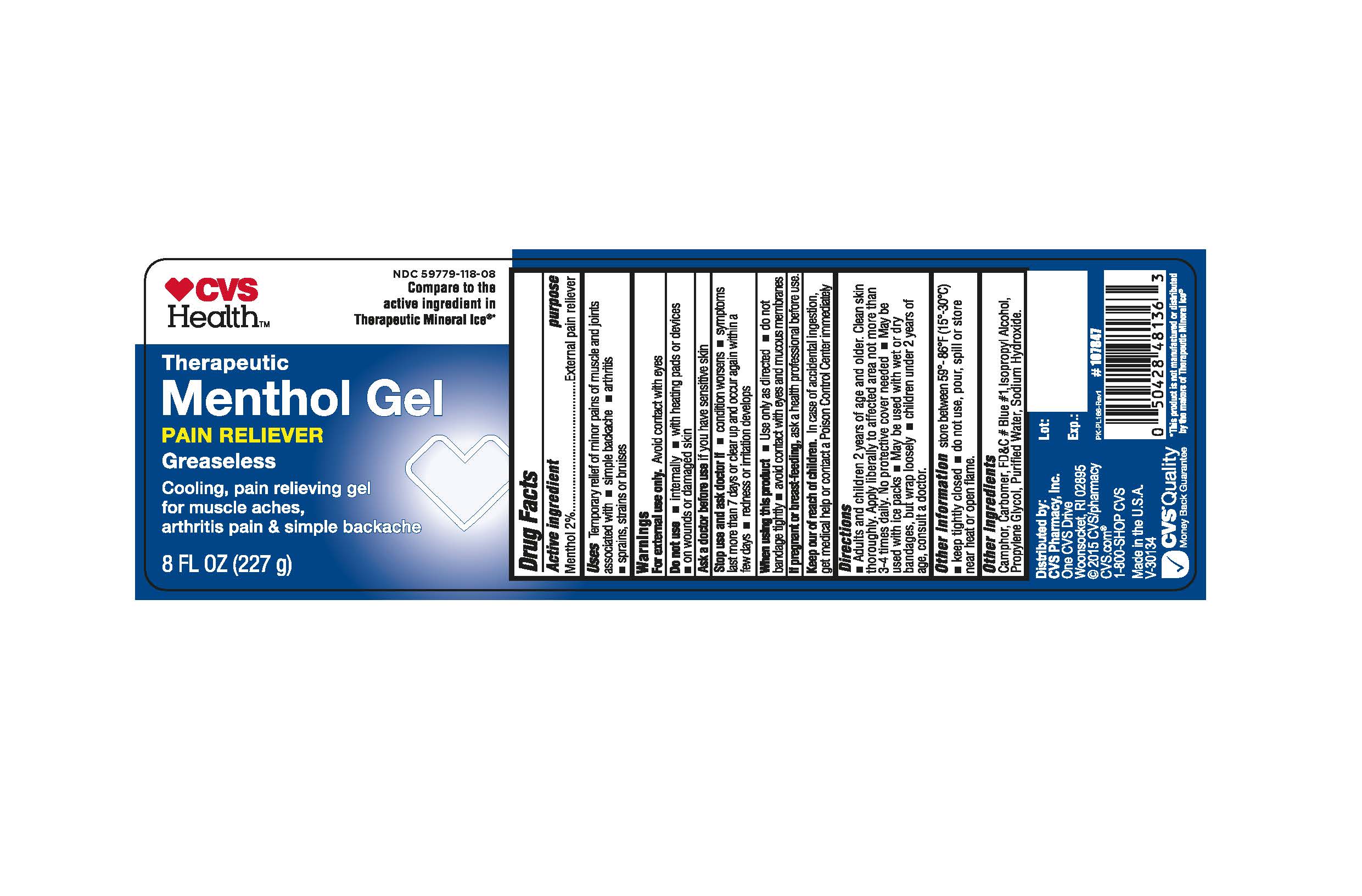 DRUG LABEL: CVS Therapeutic Menthol Gel
NDC: 59779-118 | Form: GEL
Manufacturer: CVS Pharmacy
Category: otc | Type: HUMAN OTC DRUG LABEL
Date: 20260114

ACTIVE INGREDIENTS: MENTHOL 2 g/100 g
INACTIVE INGREDIENTS: CAMPHOR (SYNTHETIC); PROPYLENE GLYCOL; ISOPROPYL ALCOHOL; SODIUM HYDROXIDE; CARBOMER HOMOPOLYMER TYPE C; FD&C BLUE NO. 1; WATER

CVS Pharmacy®Therapeutic Menthol Gel 8 oz

Active Ingredient

Active Ingredients Purpose

Menthol 2%..................................................External Pain Reliever

Purpose

Active Ingredients Purpose
Menthol 2%..................................................External Pain Reliever

Uses

Temporarily relief of minor pains of muscles and joints associated with - simple backache - arthritis - sprains, strains or bruises

Warnings

For external use only. Avoid contact with eyes

Do not use - internally - with heating pad or devices - on wounds or damaged skin

Ask a doctor before use

Ask doctor before use if you have sensitive skin

When using this product - Use only as directed - do not bandage tightly - avoid contact with eyes and mucus membranes

If pregnant or breast-feeding, ask a health professional before use.

Keep out of reach of children. In case of accidental ingestion, get medical help or contact a Poison Control Center immediately.

Directions

-Adult and children 2 years of age and older. Clean skin thoroughly. Apply liberally to affected area not more than 3-4 times daily. No protective cover needed.

-May be used with ice packs

-May be used with wet or dry bandages, but wrap loosely

-children under 2 years of age, consult a doctor

Other information

Other information store between 59o - 86oF (15o - 30oC)

-keep tightly closed - d o not use, pour, spill or store near heat or open flame.

Other ingredients

Camphor, Carbomer, FD&C #Blue #1, Isopropyl Alcohol, Propylene Glycol, Purified Water, Sodium Hydroxide.